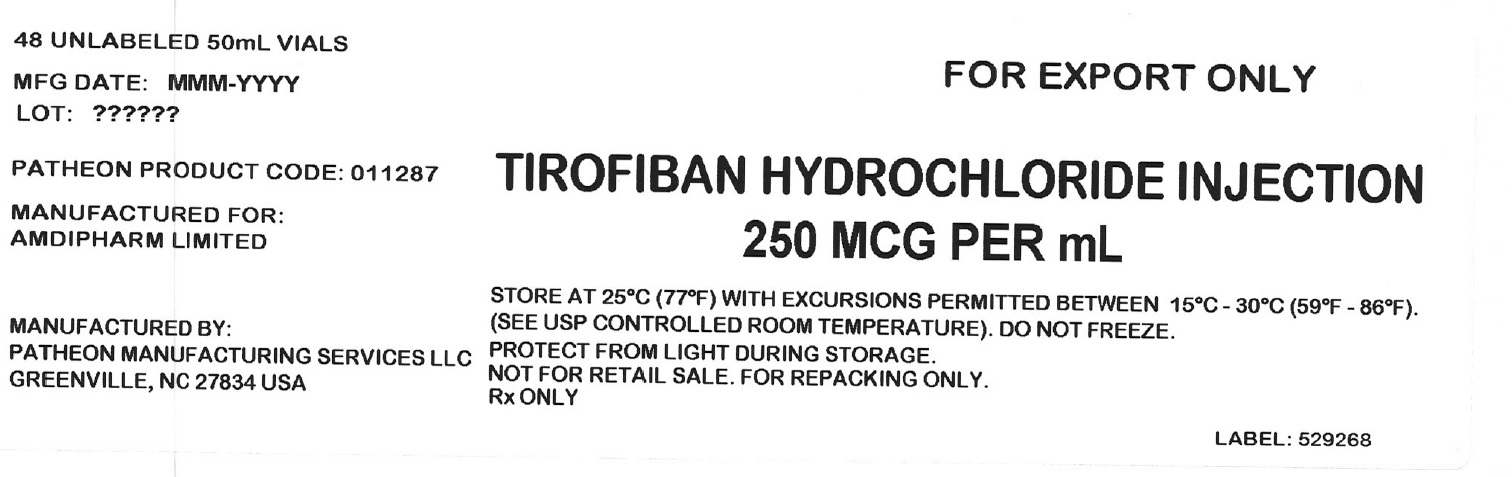 DRUG LABEL: Tirofiban Hydrochloride
NDC: 82169-025 | Form: INJECTION
Manufacturer: Amdipharm Limited
Category: other | Type: Bulk Ingredient
Date: 20220328

ACTIVE INGREDIENTS: TIROFIBAN HYDROCHLORIDE 0.25 mg/1 mL
INACTIVE INGREDIENTS: ANHYDROUS CITRIC ACID; TRISODIUM CITRATE DIHYDRATE; SODIUM CHLORIDE; WATER

TIROFIBAN HYDROCHLORIDE INJECTION

PRINCIPAL DISPLAY PANEL - Shipping Label

48 UNLABELED 50mL VIALS

MFG DATE: MMM-YYYY

LOT: ??????

PATHEON PRODUCT CODE: 011287

MANUFACTURED FOR:

AMDIPHARM LIMITED

MANUFACTURED BY:

PATHEON MANUFACTURING SERVICES LLC

GREENVILLE, NC 27834 USA

FOR EXPORT ONLY

TIROFIBAN HYDROCHLORIDE INJECTION

250 MCG PER mL

STORE AT 25°C (77°F) WITH EXCURSIONS PERMITTED BETWEEN 15°C - 30°C (59°F - 86°F).

(SEE USP CONTROLLED ROOM TEMPERATURE). DO NOT FREEZE.

PROTECT FROM LIGHT DURING STORAGE.

NOT FOR RETAIL SALE. FOR REPACKING ONLY.

Rx ONLY

LABEL: 529268